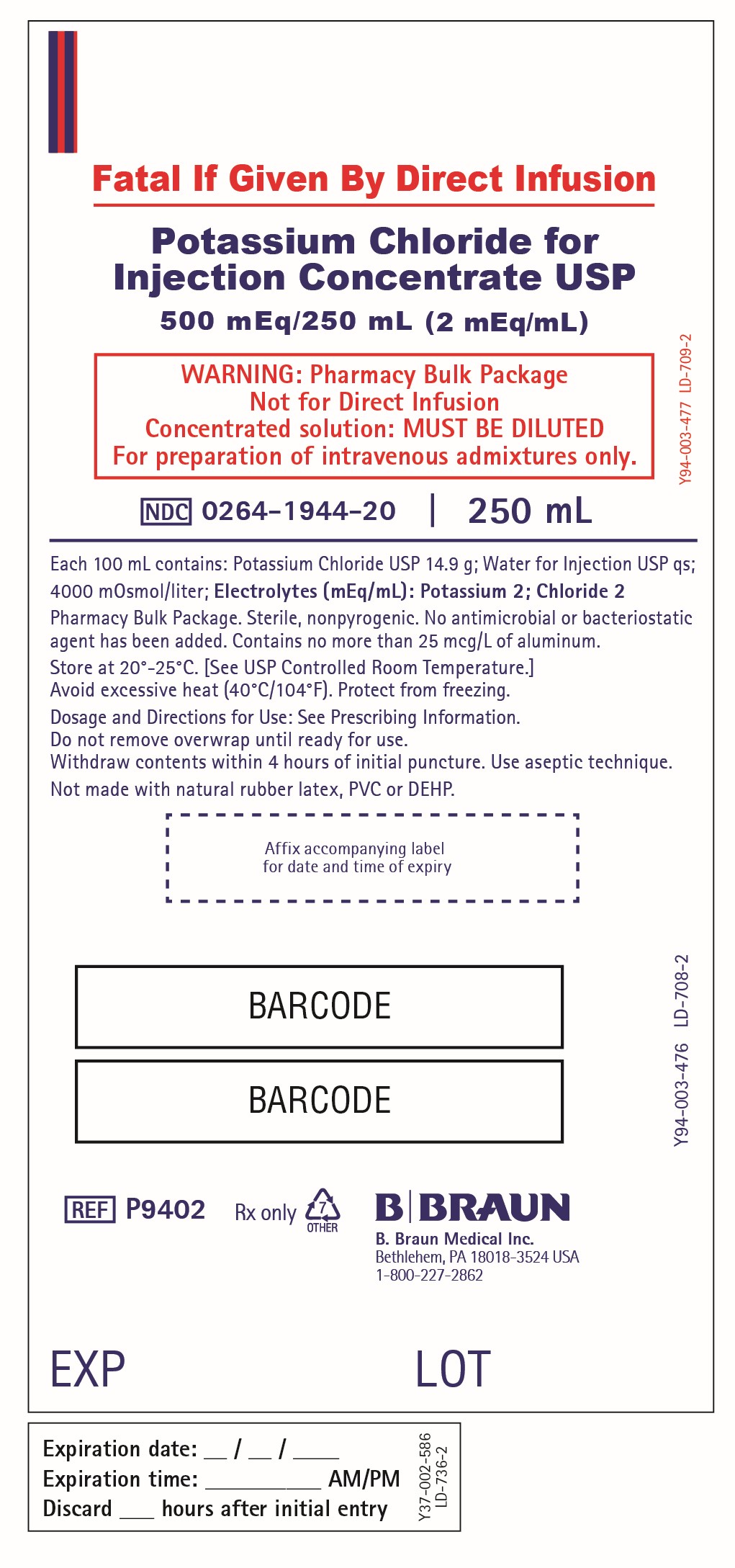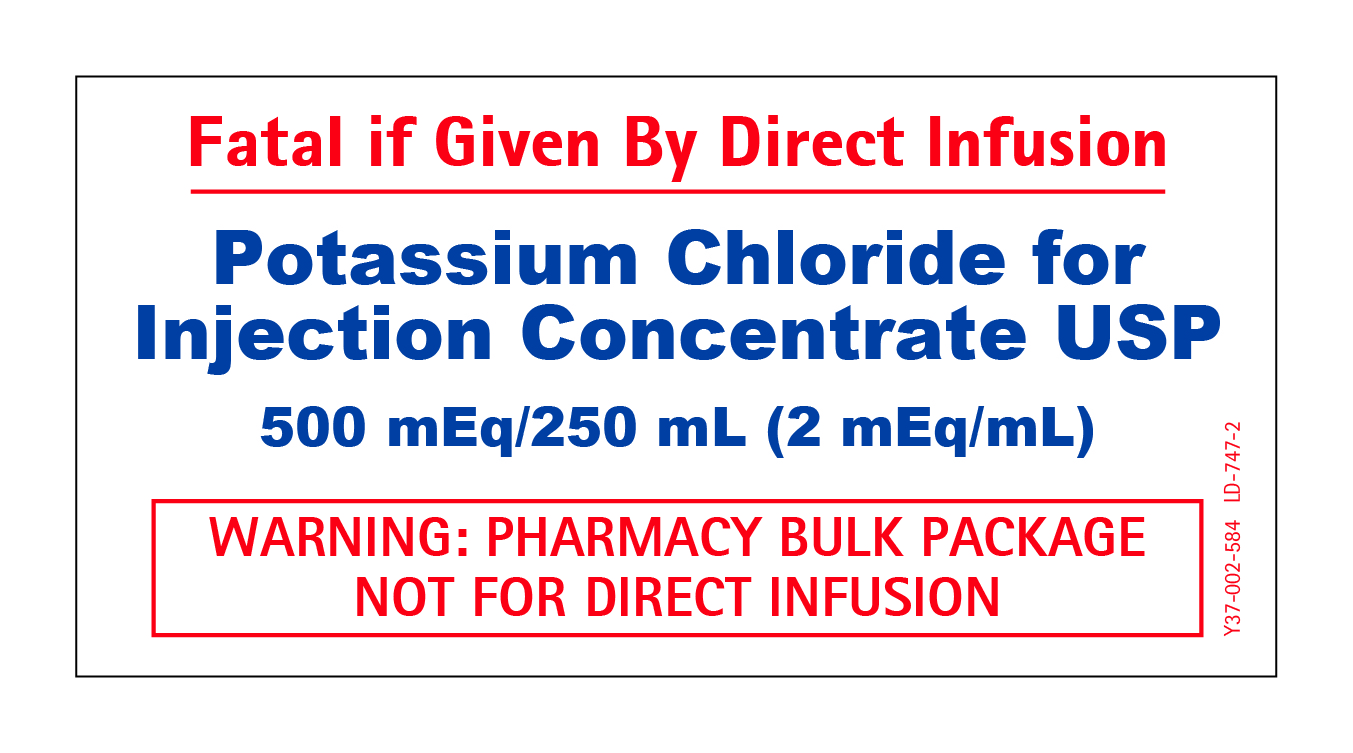 DRUG LABEL: POTASSIUM CHLORIDE
NDC: 0264-1944 | Form: INJECTION, SOLUTION, CONCENTRATE
Manufacturer: B. Braun Medical Inc.
Category: prescription | Type: HUMAN PRESCRIPTION DRUG LABEL
Date: 20220221

ACTIVE INGREDIENTS: POTASSIUM CHLORIDE 14.9 g/100 mL
INACTIVE INGREDIENTS: WATER

Potassium Chloride for Injection Concentrate USP in Excel

Y36-003-064 LD-710-2

Prescribing Information

EXCEL® CONTAINER

Potassium Chloride for Injection Concentrate USP
500 mEq/250 mL (2 mEq/mL)

PHARMACY BULK PACKAGE
NOT FOR DIRECT INFUSION

FOR INTRAVENOUS INFUSION ONLY

MUST BE DILUTED PRIOR TO INJECTION

Rx only

DESCRIPTION

A pharmacy bulk package is a container of a sterile preparation for parenteral use that contains many single doses. The contents are intended for use in a pharmacy admixture service and are restricted to the preparation of admixtures for intravenous infusion.

Potassium Chloride for Injection Concentrate USP is a sterile, nonpyrogenic, concentrated solution of Potassium Chloride USP in Water for Injection USP to be administered by intravenous infusion only after dilution in a larger volume of fluid. No bacteriostatic or antimicrobial agent has been added.

Each 100 mL of Potassium Chloride contains:

Potassium Chloride USP 14.9 g; Water for Injection USP qs

pH: 5.4 (4.0–8.0); Calculated Osmolarity: 4000 mOsmol/liter

Concentration of Electrolytes (mEq/mL): Potassium 2; Chloride 2

The formula of the active ingredient is:

Ingredient | Molecular Formula | Molecular Weight
Potassium Chloride USP | KCl | 74.55

Potassium chloride injection (approximately diluted) is a parenteral fluid and electrolyte replenisher.

Excel container not made with natural rubber latex, PVC or DEHP.

The plastic container is made from a multi-layered film specifically developed for parenteral drugs. The solution contact layer is a rubberized copolymer of ethylene and propylene. The container is nontoxic and biologically inert. The container-solution unit is a closed system and is not dependent upon entry of external air during admixing. The container is overwrapped to provide protection from the physical environment and to provide an additional moisture barrier when necessary.

The closure system has two ports; the one for the suitable transfer device or compounding set has a tamper evident plastic protector and the other is a non-accessible blocked port. Refer to the Directions for Use of the container.

CLINICAL PHARMACOLOGY

Potassium is the chief cation of body cells (160 mEq/liter of intracellular water) and is concerned with the maintenance of body fluid composition and electrolyte balance. Potassium participates in carbohydrate utilization and protein synthesis, and is critical in the regulation of nerve conduction and muscle contraction, particularly in the heart. Chloride, the major extracellular anion, closely follows the metabolism of sodium and changes in the acid-base balance of the body are reflected by changes in the chloride concentration.

Normally about 80 to 90% of the potassium intake is excreted in the urine, the remainder in the stools and to a small extent, in the perspiration. The kidney does not conserve potassium well so that during fasting, or in patients on a potassium-free diet, potassium loss from the body continues resulting in potassium depletion. A deficiency of either potassium or chloride will lead to a deficit of the other.

INDICATIONS AND USAGE

Potassium Chloride for Injection Concentrate USP is indicated in the treatment of potassium deficiency states when oral replacement is not feasible.

This is a concentrated solution which is intended for use in a pharmacy admixture service and is restricted to the preparation of admixtures for intravenous infusion.

CONTRAINDICATIONS

Potassium Chloride for Injection Concentrate USP is contraindicated in diseases where high potassium levels may be encountered, in patients with hyperkalemia, renal failure and in conditions in which potassium retention is present, or where additives of potassium and chloride could be clinically detrimental.

WARNINGS

Strongly Hypertonic Solution. Must be properly diluted and thoroughly mixed before injection.

Potentially Fatal Cardiac Adverse Reactions with Undiluted Intravenous Administration

Direct patient injection of potassium chloride at this concentration may be instantaneously fatal. Potassium Chloride for Injection Concentrate must be diluted before administration. Fatal cardiac arrhythmia and cardiac arrest have occurred when potassium chloride was administered in an undiluted form.

To avoid potassium intoxication, do not infuse these solutions rapidly. In patients with renal insufficiency, administration of potassium chloride may cause potassium intoxication and life-threatening hyperkalemia.

The administration of intravenous solutions can cause fluid and/or solute overload resulting in dilution of serum electrolyte concentrations, overhydration, congested states or pulmonary edema. The risk of dilutional states is inversely proportional to the electrolyte concentration.

The risk of solute overload causing congested states with peripheral and pulmonary edema is directly proportional to the electrolyte concentration.

In patients with diminished renal function, administration of solutions containing potassium ions may result in potassium retention.

This product contains aluminum that may be toxic. Aluminum may reach toxic levels with prolonged parenteral administration if kidney function is impaired. Premature neonates are particularly at risk because their kidneys are immature, and they require large amounts of calcium and phosphate solutions, which contain aluminum. Research indicates that patients with impaired kidney function, including premature neonates, who receive parenteral levels of aluminum at greater than 4 to 5 mcg/kg/day accumulate aluminum at levels associated with central nervous system and bone toxicity. Tissue loading may occur at even lower rates of administration.

The drug product contains no more than 25 mcg/L of aluminum.

PRECAUTIONS

General

Clinical evaluation and periodic laboratory determinations are necessary to monitor changes in fluid balance, electrolyte concentrations, and acid-base balance during prolonged parenteral therapy or whenever the condition of the patient warrants such evaluation. Significant deviations from normal concentrations may require the use of additional electrolyte supplements, or the use of electrolyte-free dextrose solutions to which individualized electrolyte supplements may be added.

Potassium therapy should be guided primarily by serial electrocardiograms, especially in patients receiving digitalis. Serum potassium levels are not necessarily indicative of tissue potassium levels. Solutions containing potassium should be used with caution in the presence of cardiac disease, particularly in the presence of renal disease, and in such instances, cardiac monitoring is recommended.

Solutions containing potassium in a greater concentration than 40 mEq/liter may result in significant irritation to peripheral or central veins.

For peripheral administration of solutions containing potassium, slowly infuse the solution through a small bore needle, placed well within the lumen of a large vein. Carefully avoid infiltration.

Solutions containing dextrose should be used with caution in patients with overt or known subclinical diabetes mellitus, or carbohydrate intolerance for any reason.

If the administration is controlled by a pumping device, care must be taken to discontinue pumping action before the container runs dry or air embolism may result.

To minimize the risk of possible incompatibilities arising from mixing this solution with other additives that may be prescribed, the final infusate should be inspected for cloudiness or precipitation immediately after mixing, prior to administration, and periodically during administration.

Use only if solution is clear and container and seals are intact. Discard container within 4 hours after initial puncture.

Pregnancy: (I) Teratogenic effects.

TERATOGENIC EFFECTS

Animal reproduction studies have not been conducted with potassium chloride injection. It is also not known whether potassium chloride injection can cause fetal harm when administered to a pregnant woman or can affect reproduction capacity. Potassium chloride injection should be given to a pregnant woman only if clearly needed.

ADVERSE REACTIONS

Reactions which may occur because of the potassium-containing solutions or the technique of administration include febrile response, infection at the site of injection, venous thrombosis or phlebitis extending from the site of injection or extravasation, hypervolemia, and hyperkalemia.

To rapid infusion of hypertonic solutions may cause local pain and, rarely, vein irritation. Rate of administration should be adjusted according to tolerance.

Reactions reported with the use of potassium-containing solutions include nausea, vomiting, abdominal pain and diarrhea. The signs and symptoms of potassium intoxication include paresthesias of the extremities, areflexia, muscular or respiratory paralysis, mental confusion, weakness, hypotension, cardiac arrhythmias, heart block, electrocardiographic abnormalities and cardiac arrest. Potassium deficits result in disruption of neuromuscular function, and intestinal ileus and dilatation.

If infused in large amounts, chloride ions may cause a loss of bicarbonate ions, resulting in an acidifying effect.

Potassium-containing solutions are intrinsically irritating to tissues. Therefore, extreme care should be taken to avoid perivascular infiltration. Local tissue necrosis and subsequent sloughing may result if extravasation occurs. Chemical phlebitis and venospasm have also been reported.

If an adverse reaction does occur, discontinue the infusion, evaluate the patient, institute appropriate therapeutic countermeasures and save the remainder of the fluid for examination if deemed necessary.

OVERDOSAGE

In the event of fluid overload during parenteral therapy, reevaluate the patient's condition and institute appropriate corrective treatment.

In the event of overdosage with potassium-containing solutions, discontinue the infusion immediately and institute corrective therapy to reduce serum potassium levels.

Treatment of hyperkalemia includes the following:

1. Dextrose Injection USP, 10% or 25%, containing 10 units of crystalline insulin per 20 grams of dextrose administered intravenously, 300 to 500 mL per hour.
2. Absorption and exchange of potassium using sodium or ammonium cycle cation exchange resin, orally and as retention enema.
3. Hemodialysis and peritoneal dialysis. The use of potassium-containing foods or medications must be eliminated. However, in cases of digitalization, too rapid a lowering of plasma potassium concentration can cause digitalis toxicity.

DOSAGE AND ADMINISTRATION

Not for direct patient injection. Potassium Chloride for Injection Concentrate USP, Pharmacy Bulk Package is for preparation of intravenous admixtures only and must be diluted before administration. Care must be taken to ensure there is complete mixing of the potassium chloride with the large volume fluid, particularly if soft or bag type containers are used.

Parenteral drug products should be inspected visually for particulate matter and discoloration prior to administration, whenever solution and container permit.

Dosage and rate of administration are to be directed by the physician and are dependent upon the specific conditions of each patient (e.g., age, weight, clinical condition of the patient and laboratory determinations). Frequent laboratory determinations and clinical evaluation are essential to monitor changes in electrolyte concentrations, and fluid and electrolyte balance during prolonged parenteral therapy.

If the serum potassium level is greater than 2.5 mEq/liter, potassium can be given at a rate not to exceed 10 mEq/hour and in a concentration of up to 40 mEq/liter. The 24 hour total dose should not exceed 200 mEq.

If urgent treatment is indicated (serum potassium level less than 2.0 mEq/liter and electrocardiographic changes and/or muscle paralysis), potassium chloride may be infused very cautiously at a rate of up to 40 mEq/hour. In such cases, continuous cardiac monitoring is essential. As much as 400 mEq may be administered in a 24 hour period. In critical conditions, potassium chloride may be administered in saline (unless contraindicated) rather than in dextrose containing fluids, as dextrose may lower serum potassium levels.

Directions for Use of Pharmacy Bulk Packages in EXCEL® Container with Blocked Medication Port

Warning: Not for direct infusion. For preparation of admixtures for intravenous infusion.

The Pharmacy Bulk Package is for use in a Pharmacy Admixture Service only. Use of this product is restricted to a suitable work area, such as a laminar flow hood (or an equivalent clean air compounding area).

Additives should not be made to Pharmacy Bulk Packages.

Caution: Do not use plastic containers in series connection.

To Open

Tear overwrap down at notch and remove solution container. Check for minute leaks by squeezing solution container firmly. If leaks are found, discard solution as sterility may be impaired.

NOTE: Before use, perform the following checks:

Inspect each container. Read the label. Ensure solution is the one ordered and is within the expiration date.

Invert container and carefully inspect the solution in good light for cloudiness, haze, or particulate matter. Any container which is suspect should not be used.

Use only if solution is clear and container and seals are intact.

Preparation for Admixing
1. Remove plastic protector from sterile set port at bottom of container.
2. Attach suitable transfer device or compounding set. Refer to complete directions accompanying device.

Do Not Add Medication
Transfer individual dose(s) to appropriate intravenous infusion solutions. Use of a syringe with needle is not recommended. Multiple entries increase the potential of microbial and particulate contamination. The container closure may be penetrated only one time, utilizing a suitable sterile dispensing set which allows measured dispensing of the contents.

For Pharmacy Bulk Packages:

- The Pharmacy Bulk Package is to be used only in a suitable work area such as a laminar air flow hood (or an equivalent clean air compounding area).
- For compounding only. Do not use for direct infusion.
- Do not use/penetrate blocked port.
- Attach suitable transfer device or compounding set. Refer to complete directions accompanying device.
- Hang container on suitable fixture.
- Once container closure has been penetrated, withdrawal of contents should be completed within 4 hours. Discard any unused portion.

Important Admixing Instructions

- The contents are intended for use in a pharmacy admixture program and are restricted to the preparation of admixtures for intravenous infusion.
- Additives may be incompatible with the fluid withdrawn from this container. Consult with pharmacist.
- When compounding admixtures, use aseptic technique, mix thoroughly and discard unused portion.
- Parenteral drug products should be inspected visually for particulate matter and discoloration prior to administration (See Warnings and Precautions, General).

HOW SUPPLIED

Potassium Chloride for Injection Concentrate USP 500 mEq/250 mL (2 mEq/mL) is supplied sterile and nonpyrogenic in 250 mL Excel® container with clear overwrap, Pharmacy Bulk Packages, packaged 24 per case.

NDC | REF | Size
Potassium Chloride for Injection Concentrate USP
0264-1944-20 | P9402 | 250 mL

STORAGE AND HANDLING

Exposure of pharmaceutical products to heat should be minimized. Store at 20° to 25°C (68° to 77°F). Avoid excessive heat (40°C/104°F). Protect from freezing. Excursions permitted 15° to 30°C (59° to 86°F). [See USP Controlled Room Temperature.]

Revised: November 2022

EXCEL is a registered trademark of B. Braun Medical Inc.

B. Braun Medical Inc.
Bethlehem, PA 18018-3524 USA
1-800-227-2862

Prepared in USA. API from Germany.

PRINCIPAL DISPLAY PANEL - 250 mL Excel® Container Label

Fatal If Given By Direct Infusion

Potassium Chloride for
Injection Concentrate USP
500 mEq/250 mL (2 mEq/mL)

WARNING: Pharmacy Bulk Package
Not for Direct Infusion
Concentrated solution: MUST BE DILUTED
For preparation of intravenous admixtures only.

Y94-003-477 LD-709-2

NDC 0264-1944-20
250 mL

Each 100 mL contains: Potassium Chloride USP 14.9 g; Water for Injection USP qs;
4000 mOsmol/liter; Electrolytes (mEq/mL): Potassium 2; Chloride 2

Pharmacy Bulk Package. Sterile, nonpyrogenic. No antimicrobial or bacteriostatic
agent has been added. Contains no more than 25 mcg/L of aluminum.

Store at 20°-25°C. [See USP Controlled Room Temperature.]
Avoid excessive heat (40°C/104°F). Protect from freezing.

Dosage and Directions for Use: See Prescribing Information.
Do not remove overwrap until ready for use.
Withdraw contents within 4 hours of initial puncture. Use aseptic technique.

Not made with natural rubber latex, PVC or DEHP.

Affix accompanying label for date and time of expiry

Expiration date: __ / __ / ____

Expiration time: ___________ AM/PM

Discard ___ hours after initial entry

Y37-002-586
LD-736-2

REF P9402

Rx only

B. Braun Medical Inc.
Bethlehem, PA 18018-3524 USA
1-800-227-2862

Y94-003-476 LD-708-2

EXP

LOT

Container Label

PRINCIPAL DISPLAY PANEL - 250 mL AUXILLARY LABEL

Fatal if Given By Direct Infusion

Potassium Chloride for
Injection Concentrate USP

500 mEq/250 mL (2 mEq/mL)

WARNING: PHARMACY BULK PACKAGE
NOT FOR DIRECT INFUSION

Y37-002-584 LD-747-2

Auxiliary Label